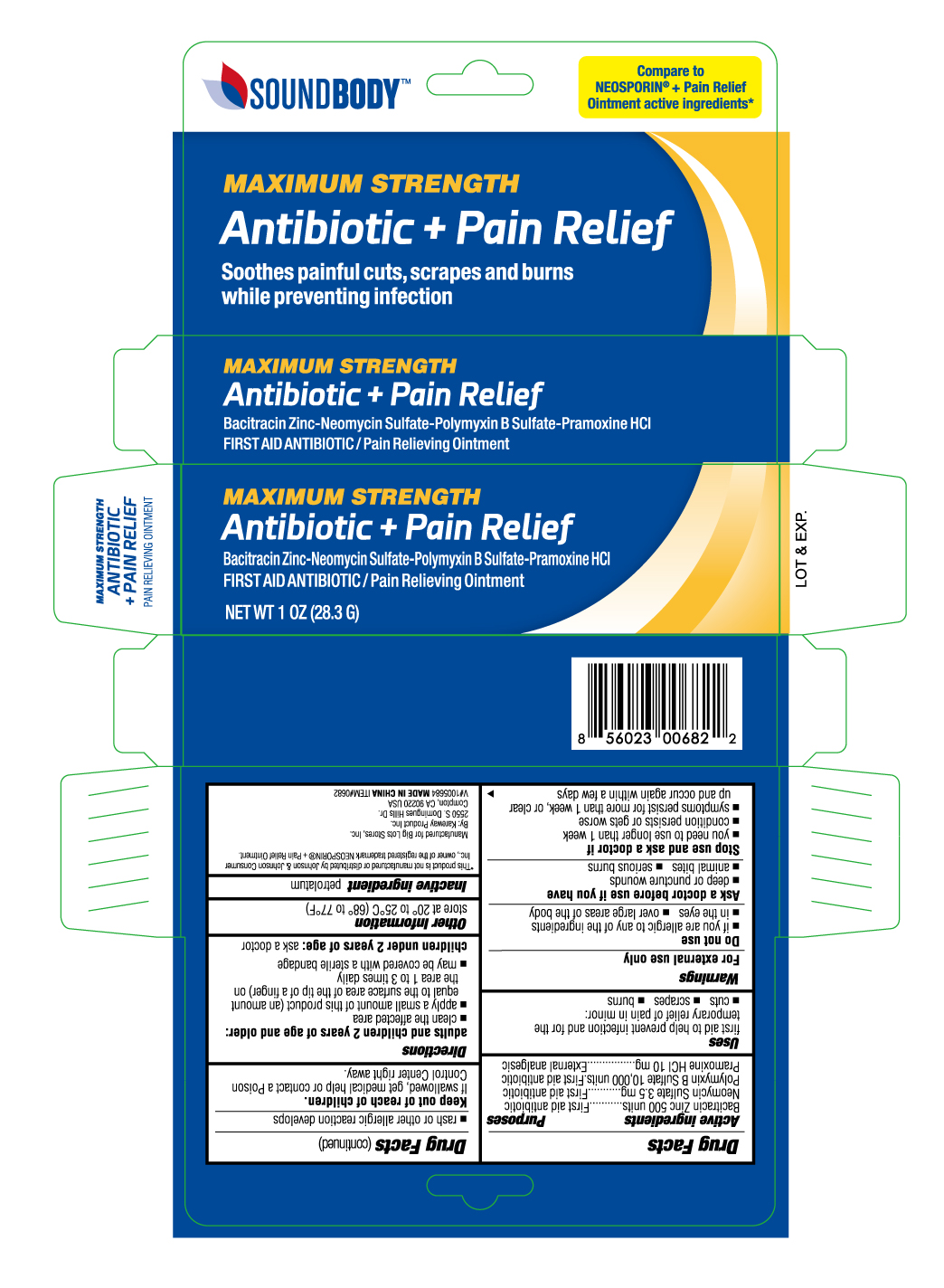 DRUG LABEL: Antibiotic Plus Pain Relief
NDC: 67510-0682 | Form: OINTMENT
Manufacturer: Kareway Product, Inc.
Category: otc | Type: HUMAN OTC DRUG LABEL
Date: 20230217

ACTIVE INGREDIENTS: NEOMYCIN SULFATE 3.5 mg/1 g; PRAMOXINE HYDROCHLORIDE 10 mg/1 g; BACITRACIN ZINC 500 [iU]/1 g; POLYMYXIN B SULFATE 10000 [iU]/1 g
INACTIVE INGREDIENTS: PETROLATUM

Soundbody Antibiotic Plus

Active Ingredients (in each gram)

Bacitracin Zinc 500units

Neomycin 3.5mg

Polymyxin B Sulfate 10,000 units

Pramoxine HCl 10mg

Purpose

Active ingredients (each gram contains) | Purpose
Bacitracin zinc 500 units | First aid antibiotic
Neomycin sulfate 3.5 mg | First aid antibiotic
Polymyxin B sulfate 10,000 units | First aid antibiotic
Pramoxine HCI 10 mg | External analgesic

Uses

First aid to help prevent infection and provide temporary relief of pain or discomfort in minor

- cuts
- scrapes
- burns

Warnings

For external use only

Do not use

- if you are allergic to any of the ingredients
- in the eyes
- over large areas of the body

Ask a doctor before use if you have

- deep or puncture wounds
- animal bites
- serious burns

Stop use and ask a doctor if

- you need to use longer than 1 week
- condition persists or gets worse
- condition persists for more than 1 week, or clear up and occur again within a few days
- a rash or other allergic reaction develops

Keep out of reach of children.

If swallowed, get medical help or contact a Poison Control Center right away.

Directions

adults and children 2 years of age and older:

- clean the affected area
- apply a small amount of this product (an amount equal to the surface area of the tip of a finger) on the area 1 to 3 times daily
- may be covered with a sterile bandage

children under 2 years of age: consult a physician

Other information

store at 20°-25°C (68°-77°F)

Inactive ingredients

petrolatum

PRINCIPAL DISPLAY PANEL

Triple Antibiotic Ointment + Pain Relief
Bacitracin Zinc • Neomycin Sulfate • Polymyxin B Sulfate • Pramoxine HCl

First Aid Antibiotic Ointment

Maximum Strength

NET WT 1 oz (28.3 g)